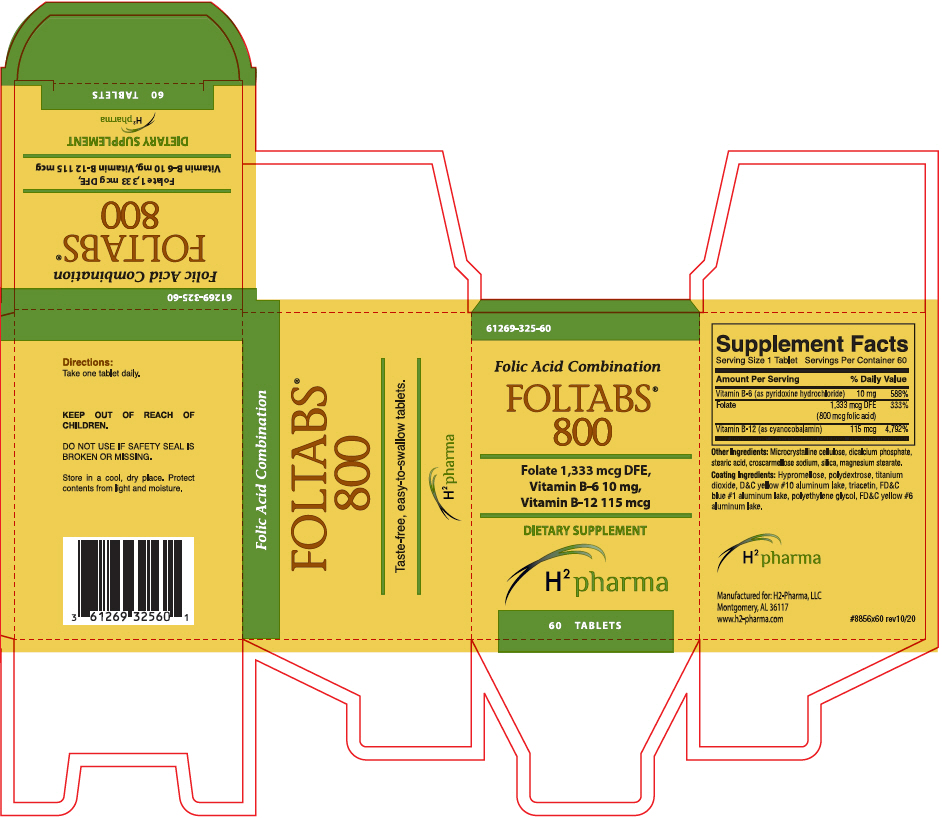 DRUG LABEL: Foltabs 800
NDC: 61269-325 | Form: TABLET
Manufacturer: H2-Pharma, LLC
Category: other | Type: DIETARY SUPPLEMENT
Date: 20220708

ACTIVE INGREDIENTS: FOLIC ACID 800 ug/1 1; CYANOCOBALAMIN 115 ug/1 1; PYRIDOXINE HYDROCHLORIDE 10 mg/1 1
INACTIVE INGREDIENTS: MICROCRYSTALLINE CELLULOSE; ANHYDROUS DIBASIC CALCIUM PHOSPHATE; STEARIC ACID; CROSCARMELLOSE SODIUM; SILICON DIOXIDE; MAGNESIUM STEARATE; HYPROMELLOSE, UNSPECIFIED; POLYDEXTROSE; TITANIUM DIOXIDE; D&C YELLOW NO. 10; TRIACETIN; FD&C BLUE NO. 1; POLYETHYLENE GLYCOL, UNSPECIFIED; FD&C YELLOW NO. 6

FOLTABS® 800

STATEMENT OF IDENTITY

Supplement Facts
Serving Size 1 Tablet | Servings Per Container 60
Amount Per Serving | % Daily Value
Vitamin B-6 (as pyridoxine hydrochloride) | 10 mg | 588%
Folate | 1,333 mcg DFE (800 mcg folic acid) | 333%
Vitamin B-12 (as cyanocobalamin) | 115 mcg | 4,792%

Other Ingredients: Microcrystalline cellulose, dicalcium phosphate, stearic acid, croscarmellose sodium, silica, magnesium stearate.

Coating Ingredients: Hypromellose, polydextrose, titanium dioxide, D&C yellow #10 aluminum lake, triacetin, FD&C blue #1 aluminum lake, polyethylene glycol, FD&C yellow #6 aluminum lake.

Directions

Take one tablet daily.

KEEP OUT OF REACH OF CHILDREN.

DO NOT USE IF SAFETY SEAL IS BROKEN OR MISSING.

HEALTH CLAIM

Store in a cool, dry place. Protect contents from light and moisture.

HEALTH CLAIM

H^2 pharma

Manufactured for: H2-Pharma, LLC
Montgomery, AL 36117
www.h2-pharma.com

#8856x60 rev10/20

PRINCIPAL DISPLAY PANEL - 60 Tablet Bottle Carton

61269-325-60

Folic Acid Combination

FOLTABS®
800

Folate 1,333 mcg DFE,
Vitamin B-6 10 mg,
Vitamin B-12 115 mcg

DIETARY SUPPLEMENT

H^2 pharma

60 TABLETS